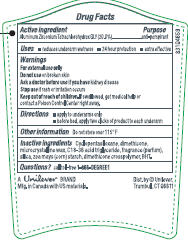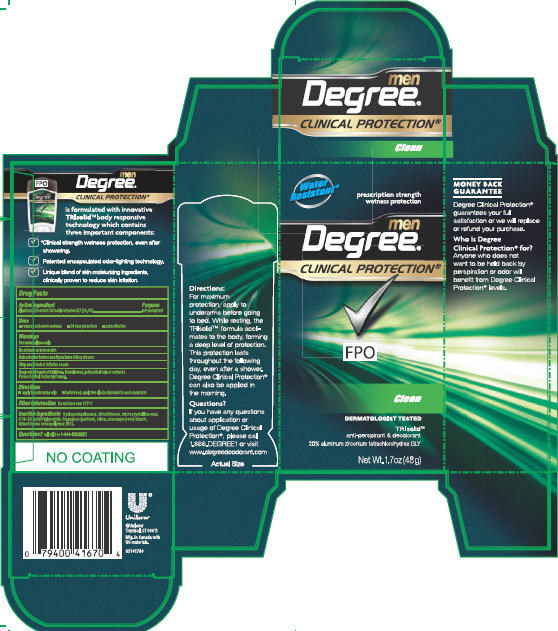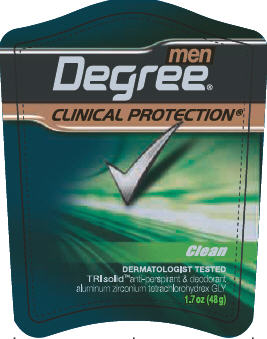 DRUG LABEL: Degree Clinical Protection Clean
NDC: 64942-1014 | Form: STICK
Manufacturer: Conopco Inc. d/b/a Unilever
Category: otc | Type: HUMAN OTC DRUG LABEL
Date: 20100518

ACTIVE INGREDIENTS: Aluminum Zirconium Tetrachlorohydrex GLY 20 g/100 g

PDPs, outer cartons and drug facts Degree Clinical Protection Clean AP/DEO

Active Ingredient Purpose

Aluminum Zirconium Tetrachlorohydrex GLY (20%).................anti-perspirant

Warnings For External Use only

Do not use on broken skin

Ask a doctor before use if you have kidney disease

Stop use if rash or irritation occurs

Keep out of reach of children. If swallowed, get medical help or contact a Poison Control Center right away.

INACTIVE INGREDIENT

Cyclopentasiloxane, Dimethicone, Microcrystalline Wax, C18-36 Acid Triglyceride, Fragrance (Parfum), Silica, Zea Mays (Corn) Starch, Dimethicone Crosspolymer, BHT.

Questions? Call toll-free 1-866-DEGREE1

PACKAGE LABEL

PDP 1.7 oz. front

PACKAGE LABEL

PDP 1.7 oz back

PACKAGE LABEL

1.7 oz carton